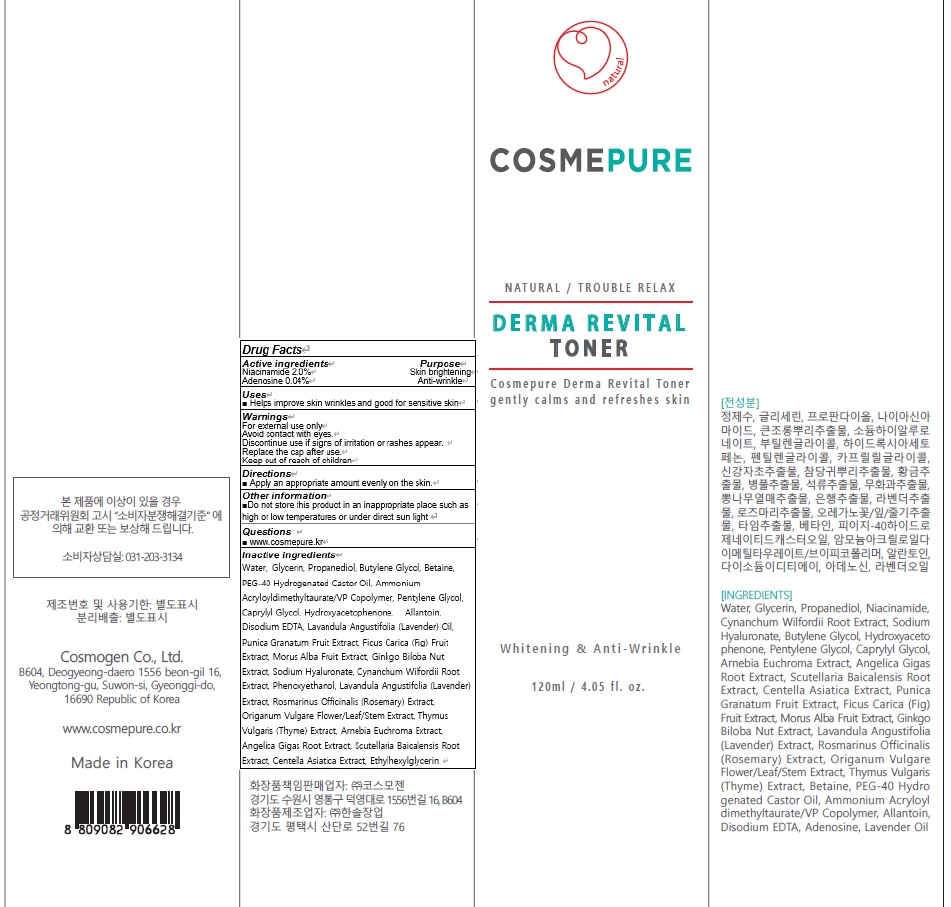 DRUG LABEL: COSMEPURE DERMA REVITAL TONER
NDC: 81418-040 | Form: LIQUID
Manufacturer: Cosmogen Co., Ltd.
Category: otc | Type: HUMAN OTC DRUG LABEL
Date: 20210129

ACTIVE INGREDIENTS: Niacinamide 2.4 g/120 mL; Adenosine 0.048 g/120 mL
INACTIVE INGREDIENTS: Water; Glycerin

ACTIVE INGREDIENTS

Niacinamide 2.0%
Adenosine 0.04%

INACTIVE INGREDIENTS

Water, Glycerin, Propanediol, Butylene Glycol, Betaine, PEG-40 Hydrogenated Castor Oil, Ammonium Acryloyldimethyltaurate/VP Copolymer, Pentylene Glycol, Caprylyl Glycol, Hydroxyacetophenone, Allantoin, Disodium EDTA, Lavandula Angustifolia (Lavender) Oil, Punica Granatum Fruit Extract, Ficus Carica (Fig) Fruit Extract, Morus Alba Fruit Extract, Ginkgo Biloba Nut Extract, Sodium Hyaluronate, Cynanchum Wilfordii Root Extract, Phenoxyethanol, Lavandula Angustifolia (Lavender) Extract, Rosmarinus Officinalis (Rosemary) Extract, Origanum Vulgare Flower/Leaf/Stem Extract, Thymus Vulgaris (Thyme) Extract, Arnebia Euchroma Extract, Angelica Gigas Root Extract, Scutellaria Baicalensis Root Extract, Centella Asiatica Extract, Ethylhexylglycerin

PURPOSE

Skin brightening
Anti wrinkle

WARNINGS

For external use only
Avoid contact with eyes.
Discontinue use if signs of irritation or rashes appear.
Replace the cap after use.
Keep out of reach of children

KEEP OUT OF REACH OF CHILDREN

Uses

■ Helps improve skin wrinkles and good for sensitive skin

Directions

■ Apply an appropriate amount evenly on the skin.

Other information

■ Do not store this product in an inappropriate place such as high or low temperatures or under direct sun light

QUESTIONS

■ www.cosmepure.kr